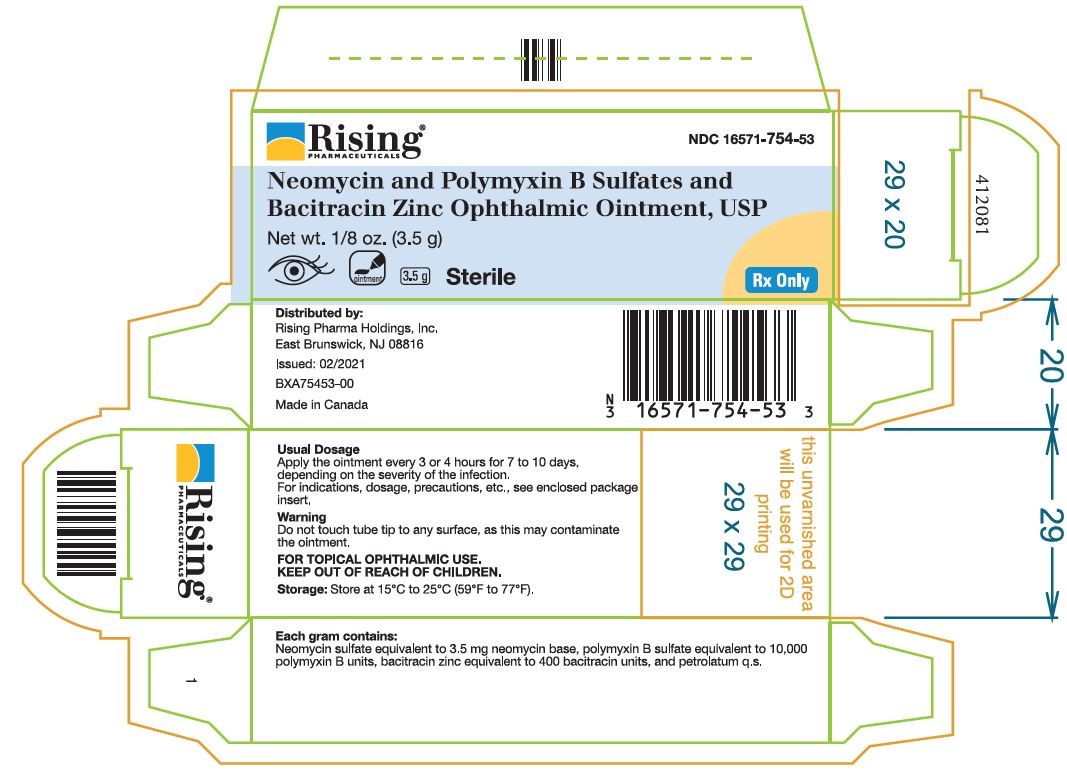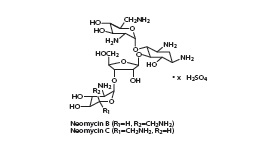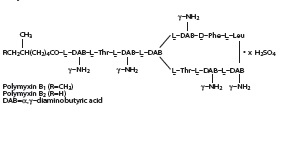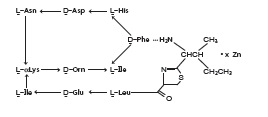 DRUG LABEL: Neomycin and Polymyxin B Sulfates and Bacitracin Zinc
NDC: 16571-754 | Form: OINTMENT
Manufacturer: Rising Pharma Holdings, Inc.
Category: prescription | Type: Human Prescription Drug Label
Date: 20211115

ACTIVE INGREDIENTS: NEOMYCIN SULFATE 3.5 mg/1 g; POLYMYXIN B SULFATE 10000 [USP'U]/1 g; BACITRACIN ZINC 400 [USP'U]/1 g
INACTIVE INGREDIENTS: PETROLATUM

Neomycin and Polymyxin B Sulfates and Bacitracin Zinc Ophthalmic Ointment, USP Sterile

DESCRIPTION

Neomycin and Polymyxin B Sulfates and Bacitracin Zinc Ophthalmic Ointment, USP is a sterile antimicrobial ointment for topical ophthalmic use. Each gram contains: neomycin sulfate equivalent to 3.5 mg neomycin base, polymyxin B sulfate equivalent to 10,000 polymyxin B units, and bacitracin zinc equivalent to 400 bacitracin units and petrolatum q.s.
Neomycin sulfate is the sulfate salt of neomycin B and C, which are produced by the growth of Streptomyces fradiae Waksman (Fam. Streptomycetaceae). It has a potency equivalent of not less than 600 micrograms of neomycin standard per mg, calculated on an anhydrous basis. The structural formulae are:

Polymyxin B sulfate is the sulfate salt of polymyxin B1 and B2 which are produced by the growth of Bacillus polymyxa (Prazmowski) Migula (Fam. Bacillaceae). It has a potency of not less than 6,000 polymyxin B units per mg, calculated on an anhydrous basis. The structural formulae are:

Bacitracin zinc is the zinc salt of bacitracin, a mixture of related cyclic polypeptides (mainly bacitracin A) produced by the growth of an organism of the licheniformis group of Bacillus subtilis var Tracy. It has a potency of not less than 40 bacitracin units per mg. The structural formula is:

CLINICAL PHARMACOLOGY

A wide range of antibacterial action is provided by the overlapping spectra of neomycin, polymyxin B sulfate, and bacitracin.

Neomycin is bactericidal for many gram-positive and gram-negative organisms. It is an aminoglycoside antibiotic which inhibits protein synthesis by binding with ribosomal RNA and causing misreading of the bacterial genetic code.

Polymyxin B is bactericidal for a variety of gram-negative organisms. It increases the permeability of the bacterial cell membrane by interacting with the phospholipid components of the membrane.

Bacitracin is bactericidal for a variety of gram-positive and gram-negative organisms. It interferes with bacterial cell wall synthesis by inhibition of the regeneration of phospholipid receptors involved in peptidoglycan synthesis.

Microbiology

Neomycin sulfate, polymyxin B sulfate and bacitracin zinc together are considered active against the following microorganisms: Staphylococcus aureus, streptococci including Streptococcus pneumoniae, Escherichia coli, Haemophilus influenzae, Klebsiella/Enterobacter species, Neisseria species, and Pseudomonas aeruginosa. The product does not provide adequate coverage against Serratia marcescens.

INDICATIONS & USAGE

Neomycin and polymyxin B sulfates and bacitracin zinc ophthalmic ointment is indicated for the topical treatment of superficial infections of the external eye and its adnexa caused by susceptible bacteria. Such infections encompass conjunctivitis, keratitis and keratoconjunctivitis, blepharitis and blepharoconjunctivitis.

CONTRAINDICATIONS

Neomycin and polymyxin B sulfates and bacitracin zinc ophthalmic ointment is contraindicated in individuals who have shown hypersensitivity to any of its components.

WARNINGS

NOT FOR INJECTION INTO THE EYE. Neomycin and polymyxin B sulfates and bacitracin zinc ophthalmic ointment should never be directly introduced into the anterior chamber of the eye. Ophthalmic ointments may retard corneal wound healing.
Topical antibiotics, particularly neomycin sulfate, may cause cutaneous sensitization. A precise incidence of hypersensitivity reactions (primarily skin rash) due to topical antibiotics is not known. The manifestations of sensitization to topical antibiotics are usually itching, reddening, and edema of the conjunctiva and eyelid. A sensitization reaction may manifest simply as a failure to heal. During long-term use of topical antibiotic products, periodic examination for such signs is advisable, and the patient should be told to discontinue the product if they are observed. Symptoms usually subside quickly on withdrawing the medication. Application of products containing these ingredients should be avoided for the patient thereafter (see PRECAUTIONS: General).

PRECAUTIONS

GENERAL

As with other antibiotic preparations, prolonged use of neomycin and polymyxin B sulfates and bacitracin zinc ophthalmic ointment may result in overgrowth of nonsusceptible organisms including fungi. If superinfection occurs, appropriate measures should be initiated.

Bacterial resistance to neomycin and polymyxin B sulfates and bacitracin zinc ophthalmic ointment may also develop. If purulent discharge, inflammation, or pain becomes aggravated, the patient should discontinue use of the medication and consult a physician.

There have been reports of bacterial keratitis associated with the use of topical ophthalmic products in multiple-dose containers which have been inadvertently contaminated by patients, most of whom had a concurrent corneal disease or a disruption of the ocular epithelial surface (see PRECAUTIONS: Information for Patients).

Allergic cross-reactions may occur which could prevent the use of any or all of the following antibiotics for the treatment of future infections: kanamycin, paromomycin, streptomycin, and possibly gentamicin.

INFORMATION FOR PATIENTS

Patients should be instructed to avoid allowing the tip of the dispensing container to contact the eye, eyelid, fingers, or any other surface. The use of this product by more than one person may spread infection.
Patients should also be instructed that ocular products, if handled improperly, can become contaminated by common bacteria known to cause ocular infections. Serious damage to the eye and subsequent loss of vision may result from using contaminated products (see PRECAUTIONS: General).
If the condition persists or gets worse, or if a rash or allergic reaction develops, the patient should be advised to stop use and consult a physician. Do not use this product if you are allergic to any of the listed ingredients.
Keep tightly closed when not in use. Keep out of reach of children.

CARCINOGENESIS & MUTAGENESIS & IMPAIRMENT OF FERTILITY

Long-term studies in animals to evaluate carcinogenic or mutagenic potential have not been conducted with polymyxin B sulfate or bacitracin. Treatment of cultured human lymphocytes in vitro with neomycin increased the frequency of chromosome aberrations at the highest concentration (80 mcg/mL) tested; however, the effects of neomycin on carcinogenesis and mutagenesis in humans are unknown.
Polymyxin B has been reported to impair the motility of equine sperm, but its effects on male or female fertility are unknown. No adverse effects on male or female fertility, litter size or survival were observed in rabbits given bacitracin zinc 100 gm/ton of diet.

PREGNANCY

Teratogenic Effects: Animal reproduction studies have not been conducted with neomycin sulfate, polymyxin B sulfate, or bacitracin. It is also not known whether neomycin and polymyxin B sulfates and bacitracin zinc ophthalmic ointment can cause fetal harm when administered to a pregnant woman or can affect reproduction capacity. Neomycin and polymyxin B sulfates and bacitracin zinc ophthalmic ointment should be given to a pregnant woman only if clearly needed.

NURSING MOTHERS

It is not known whether this drug is excreted in human milk. Because many drugs are excreted in human milk, caution should be exercised when neomycin and polymyxin B sulfates and bacitracin zinc ophthalmic ointment is administered to a nursing woman.

PEDIATRIC USE

Safety and effectiveness in children have not been established.

GERIATRIC USE

No overall differences in safety or effectiveness have been observed between elderly and younger patients.

ADVERSE REACTIONS

Adverse reactions have occurred with the anti-infective components of neomycin and polymyxin B sulfates and bacitracin zinc ophthalmic ointment. The exact incidence is not known. Reactions occurring most often are allergic sensitization reactions including itching, swelling, and conjunctival erythema (see WARNINGS). More serious hypersensitivity reactions, including anaphylaxis, have been reported rarely.

Local irritation on instillation has also been reported.

To report SUSPECTED ADVERSE REACTIONS, contact Rising Pharma Holdings, Inc. at (1-844-874-7464) or FDA at 1-800-FDA-1088 or www.fda.gov/medwatch.

DOSAGE & ADMINISTRATION

Apply the ointment topically into the conjunctival sac of the affected eye(s) every 3 or 4 hours for 7 to 10 days, depending on the severity of the infection.

HOW SUPPLIED

Neomycin and Polymyxin B Sulfates and Bacitracin Zinc Ophthalmic Ointment, USP is supplied in a tube of 1/8 oz (3.5 g) with an ophthalmic tip (NDC 16571-754-53).
Caution: Federal law prohibits dispensing without a prescription.
Store at 15°C to 25°C (59°F to 77°F).
FOR TOPICAL OPHTHALMIC USE
Distributed by:
Rising Pharma Holdings, Inc.
East Brunswick, NJ 08816
Issued: 02/2021
PIA75453-00
Made in Canada

PACKAGE LABEL.PRINCIPAL DISPLAY PANEL

Rising® NDC 16571-754-53
Neomycin and Polymyxin B Sulfates and
Bacitracin Zinc Ophthalmic Ointment, USP
Net wt. 1/8 oz. (3.5g)
Sterile Rx Only